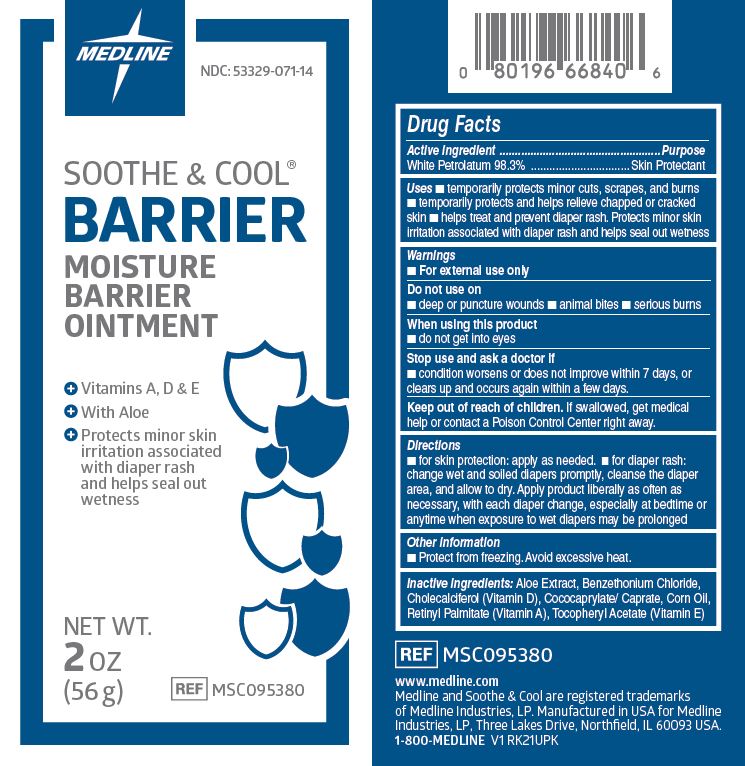 DRUG LABEL: Soothe and Cool Moisture Barrier
NDC: 53329-071 | Form: OINTMENT
Manufacturer: Medline Industries, LP
Category: otc | Type: HUMAN OTC DRUG LABEL
Date: 20241126

ACTIVE INGREDIENTS: PETROLATUM 98.3 g/100 g
INACTIVE INGREDIENTS: CHOLECALCIFEROL; BENZETHONIUM CHLORIDE; CORN OIL; VITAMIN A PALMITATE; .ALPHA.-TOCOPHEROL ACETATE, D-; COCO-CAPRYLATE/CAPRATE; ALOE

071 Soothe & Cool Moisture Barrier Ointment

Active ingredient

White Petrolatum 98.3%

Purpose

Skin Protectant

Uses

- temporarily protects minor: cuts, scrapes, burns
- temporarily protects and helps relieve chapped or cracked skin
- helps treat and prevent diaper rash. Protects minor skin irritation associated with diaper rash and helps seal out wetness

Warnings

For external use only.

Do not use on

- deep or puncture wounds
- animal bites
- serious burns

When using this product

- do not get into eyes

Stop use and ask a doctor if

- condition worsens or does not improve within 7 days, or clears up and occurs again within a few days

Keep out of reach of children.

If swallowed, get medical help or contact a Poison Control Center right away.

Directions

- for skin protection: apply as needed
- for diaper rash: change wet and soiled diapers promptly, cleanse the diaper area, and allow to dry. Apply product liberally as often as necessary, with each diaper change, especially at bedtime or anytime when exposure to wet diapers may be prolonged

Inactive ingredients

aloe extract, benzethonium chloride, cholecalciferol (vitamin D), cococaprylate /caprate, corn oil, retinyl palmitate (vitamin A), tocopheryl acetate (vitamin E)

Manufacturing Information

Manufactured for:

Medline Industries, LP

Three Lakes Drive, Northfield, IL 60093 USA

www.medline.com

1-800-MEDLINE (633-5463)

REF: MSC095380

V1 RK21UPK